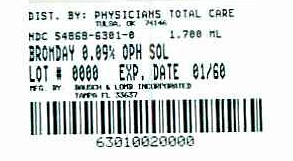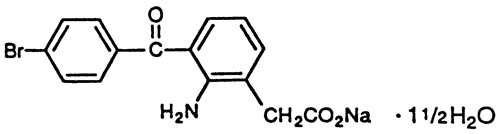 DRUG LABEL: Bromday
NDC: 54868-6301 | Form: SOLUTION/ DROPS
Manufacturer: Physicians Total Care, Inc.
Category: prescription | Type: HUMAN PRESCRIPTION DRUG LABEL
Date: 20100914

ACTIVE INGREDIENTS: BROMFENAC SODIUM 0.9 mg/1 mL
INACTIVE INGREDIENTS: BENZALKONIUM CHLORIDE 0.05 mg/1 mL; BORIC ACID; EDETATE DISODIUM; POLYSORBATE 80; POVIDONE; SODIUM BORATE; SODIUM SULFITE; SODIUM HYDROXIDE; WATER

HIGHLIGHTS OF PRESCRIBING INFORMATION

These highlights do not include all the information needed to use Bromday™ (bromfenac ophthalmic solution) 0.09% safely and effectively. See full prescribing information for Bromday.
Bromday (bromfenac ophthalmic solution) 0.09%
Initial U.S. Approval: 1997

1 INDICATIONS AND USAGE

Bromday is a nonsteroidal anti-inflammatory drug (NSAID) indicated for the treatment of postoperative inflammation and reduction of ocular pain in patients who have undergone cataract extraction (1).

2 DOSAGE AND ADMINISTRATION

Instill one drop into the affected eye(s) once daily beginning 1 day prior to surgery, continued on the day of surgery and through the first 14 days post-surgery (2.1).

3 DOSAGE FORMS AND STRENGTHS

Topical ophthalmic solution: bromfenac 0.09% (3).

5 WARNINGS AND PRECAUTIONS

- Sulfite Allergic Reactions (5.1)
- Slow or Delayed Healing (5.2)
- Potential for cross-sensitivity (5.3)
- Increase bleeding of ocular tissues (5.4)
- Corneal effects including keratitis (5.5)
- Contact Lens Wear (5.6)

6 ADVERSE REACTIONS

The most commonly reported adverse reactions in 2-7% of patients were abnormal sensation in eye, conjunctival hyperemia and eye irritation (including burning/stinging) (6.1).

To report SUSPECTED ADVERSE REACTIONS, contact ISTA Pharmaceuticals, Inc. at 1-877-788-2020, or FDA at 1-800-FDA-1088 or www.fda.gov/medwatch.

FULL PRESCRIBING INFORMATION

1 INDICATIONS AND USAGE

Bromday™ (bromfenac ophthalmic solution) 0.09% is indicated for the treatment of postoperative inflammation and reduction of ocular pain in patients who have undergone cataract surgery.

2 DOSAGE AND ADMINISTRATION

2.1 Recommended Dosing

For the treatment of postoperative inflammation in patients who have undergone cataract extraction, one drop of Bromday ophthalmic solution should be applied to the affected eye(s) once daily beginning 1 day prior to cataract surgery, continued on the day of surgery, and through the first 14 days of the postoperative period.

2.2 Use with Other Topical Ophthalmic Medications

Bromday ophthalmic solution may be administered in conjunction with other topical ophthalmic medications such as alpha-agonists, beta-blockers, carbonic anhydrase inhibitors, cycloplegics, and mydriatics. Drops should be administered at least 5 minutes apart.

3 DOSAGE FORMS AND STRENGTHS

Topical ophthalmic solution: bromfenac 0.09%.

4 CONTRAINDICATIONS

None.

5 WARNINGS AND PRECAUTIONS

5.1 Sulfite Allergic Reactions

Contains sodium sulfite, a sulfite that may cause allergic-type reactions including anaphylactic symptoms and life-threatening or less severe asthmatic episodes in certain susceptible people. The overall prevalence of sulfite sensitivity in the general population is unknown and probably low. Sulfite sensitivity is seen more frequently in asthmatic than in non-asthmatic people.

5.2 Slow or Delayed Healing

All topical nonsteroidal anti-inflammatory drugs (NSAIDs) may slow or delay healing. Topical corticosteroids are also known to slow or delay healing. Concomitant use of topical NSAIDs and topical steroids may increase the potential for healing problems

5.3 Potential for Cross-Sensitivity

There is the potential for cross-sensitivity to acetylsalicylic acid, phenylacetic acid derivatives, and other NSAIDs. Therefore, caution should be used when treating individuals who have previously exhibited sensitivities to these drugs.

5.4 Increased Bleeding Time

With some NSAIDs, there exists the potential for increased bleeding time due to interference with platelet aggregation. There have been reports that ocularly applied NSAIDs may cause increased bleeding of ocular tissues (including hyphemas) in conjunction with ocular surgery.

It is recommended that Bromday ophthalmic solution be used with caution in patients with known bleeding tendencies or who are receiving other medications which may prolong bleeding time.

5.5 Keratitis and Corneal Reactions

Use of topical NSAIDs may result in keratitis. In some susceptible patients, continued use of topical NSAIDs may result in epithelial breakdown, corneal thinning, corneal erosion, corneal ulceration or corneal perforation. These events may be sight threatening. Patients with evidence of corneal epithelial breakdown should immediately discontinue use of topical NSAIDs and should be closely monitored for corneal health.

Post-marketing experience with topical NSAIDs suggests that patients with complicated ocular surgeries, corneal denervation, corneal epithelial defects, diabetes mellitus, ocular surface diseases (e.g., dry eye syndrome), rheumatoid arthritis, or repeat ocular surgeries within a short period of time may be at increased risk for corneal adverse events which may become sight threatening. Topical NSAIDs should be used with caution in these patients.

Post-marketing experience with topical NSAIDs also suggests that use more than 24 hours prior to surgery or use beyond 14 days post surgery may increase patient risk for the occurrence and severity of corneal adverse events.

5.6 Contact Lens Wear

Bromday should not be administered while wearing contact lenses.

6 ADVERSE REACTIONS

6.1 Clinical Trial Experience

The most commonly reported adverse experiences reported following use of bromfenac after cataract surgery include: abnormal sensation in eye, conjunctival hyperemia, eye irritation (including burning/stinging), eye pain, eye pruritus, eye redness, headache, and iritis. These events were reported in 2-7% of patients.

6.2 Post-Marketing Experience

The following events have been identified during post-marketing use of bromfenac ophthalmic solution 0.09% in clinical practice. Because they are reported voluntarily from a population of unknown size, estimates of frequency cannot be made. The events, which have been chosen for inclusion due to either their seriousness, frequency of reporting, possible causal connection to topical bromfenac ophthalmic solution 0.09% or a combination of these factors, include corneal erosion, corneal perforation, corneal thinning, and epithelial breakdown. [see Warnings and Precautions (5)]

8 USE IN SPECIFIC POPULATIONS

8.1 Pregnancy

Teratogenic Effects: Pregnancy Category C. Reproduction studies performed in rats at oral doses up to 0.9 mg/kg/day (1300 times the recommended human ophthalmic dose [RHOD]) and in rabbits at oral doses up to 7.5 mg/kg/day (11,000 times RHOD) revealed no evidence of teratogenicity due to bromfenac. However, 0.9 mg/kg/day in rats caused embryo-fetal lethality, increased neonatal mortality, and reduced postnatal growth. Pregnant rabbits treated with 7.5 mg/kg/day caused increased post-implantation loss.

There are no adequate and well-controlled studies in pregnant women. Because animal reproduction studies are not always predictive of human response, this drug should be used during pregnancy only if the potential benefit justifies the potential risk to the fetus.

Nonteratogenic Effects:

Because of the known effects of prostaglandin biosynthesis-inhibiting drugs on the fetal cardiovascular system (closure of ductus arteriosus), the use of Bromday ophthalmic solution during late pregnancy should be avoided.

8.3 Nursing Mothers

Caution should be exercised when Bromday is administered to a nursing woman.

8.4 Pediatric Use

Safety and efficacy in pediatric patients below the age of 18 have not been established.

8.5 Geriatric Use

There is no evidence that the efficacy or safety profiles for Bromday differ in patients 65 years of age and older compared to younger adult patients.

11 DESCRIPTION

Bromday™ (bromfenac ophthalmic solution) 0.09% is a sterile, topical, nonsteroidal anti-inflammatory drug (NSAID) for ophthalmic use. Each mL of Bromday contains 1.035 mg bromfenac sodium (equivalent to 0.9 mg bromfenac free acid). Bromfenac sodium is designated chemically as sodium 2-amino-3-(4-bromobenzoyl) phenylacetate sesquihydrate, with an empirical formula of C15H11BrNNaO3• 1½H2O. The structural formula for bromfenac sodium is:

Bromfenac sodium is a yellow to orange crystalline powder. The molecular weight of bromfenac sodium is 383.17. Bromday ophthalmic solution is supplied as a sterile aqueous 0.09% solution, with a pH of 8.3. The osmolality of Bromday ophthalmic solution is approximately 300 mOsmol/kg.

Each mL of Bromday ophthalmic solution contains:
Active: bromfenac sodium hydrate 0.1035%
Preservative: benzalkonium chloride (0.05 mg/mL)
Inactives: boric acid, disodium edetate (0.2 mg/mL), polysorbate 80 (1.5 mg/mL), povidone (20 mg/mL), sodium borate, sodium sulfite anhydrous (2 mg/mL), sodium hydroxide to adjust pH and water for injection, USP.

12 CLINICAL PHARMACOLOGY

12.1 Mechanism of Action

Bromfenac is a nonsteroidal anti-inflammatory drug (NSAID) that has anti-inflammatory activity. The mechanism of its action is thought to be due to its ability to block prostaglandin synthesis by inhibiting cyclooxygenase 1 and 2.

Prostaglandins have been shown in many animal models to be mediators of certain kinds of intraocular inflammation. In studies performed in animal eyes, prostaglandins have been shown to produce disruption of the blood-aqueous humor barrier, vasodilation, increased vascular permeability, leukocytosis, and increased intraocular pressure.

12.3 Pharmacokinetics

The plasma concentration of bromfenac following ocular administration of 0.09% Bromday (bromfenac ophthalmic solution) in humans is unknown. Based on the maximum proposed dose of one drop to the eye (0.045 mg) and PK information from other routes of administration, the systemic concentration of bromfenac is estimated to be below the limit of quantification (50 ng/mL) at steady-state in humans.

13 NONCLINICAL TOXICOLOGY

13.1 Carcinogenesis, Mutagenesis and Impairment of Fertility

Long-term carcinogenicity studies in rats and mice given oral doses of bromfenac up to 0.6 mg/kg/day (900 times the recommended human ophthalmic dose [RHOD] of 1.67 mcg/kg in 60 kg person on a mg/kg/basis, assuming 100% absorbed) and 5 mg/kg/day (7500 times RHOD), respectively revealed no significant increases in tumor incidence.

Bromfenac did not show mutagenic potential in various mutagenicity studies, including the reverse mutation, chromosomal aberration, and micronucleus tests.

Bromfenac did not impair fertility when administered orally to male and female rats at doses up to 0.9 mg/kg/day and 0.3 mg/kg/day, respectively (1300 and 450 times RHOD, respectively).

14 CLINICAL STUDIES

14.1 Ocular inflammation and pain following cataract surgery

Clinical efficacy was evaluated in three randomized, double-masked, placebo-controlled trials in which subjects requiring cataract surgery were assigned to Bromday or placebo. Patients were dosed with one drop per eye starting the day before surgery and continuing for 14 days. The primary endpoint was clearing of ocular inflammation by day 15. An additional efficacy endpoint was the number of patients who were pain free on day 1 after cataract surgery.

In 2 of the 3 studies, Bromday ophthalmic solution had statistically significant higher incidence of completely clearing inflammation (46-47% vs. 25-29%) and also had a statistically significant higher incidence of subjects that were pain free at day 1 post cataract surgery (83-89% vs. 51-71%).

16 HOW SUPPLIED/STORAGE AND HANDLING

Bromday (bromfenac ophthalmic solution) 0.09% is supplied in a white LDPE plastic squeeze bottle with a 15 mm LDPE white dropper-tip and 15 mm polypropylene gray cap as follows:

1.7 mL in 7.5 mL container (NDC 54868-6301-0)

STORAGE

Store at 15º – 25ºC (59º – 77ºF).

17 PATIENT COUNSELING INFORMATION

17.1 Slowed or Delayed Healing

Patients should be advised of the possibility that slow or delayed healing may occur while using NSAIDs.

17.2 Sterility of Dropper Tip

Patients should be advised to not touch dropper tip to any surface, as this may contaminate the contents.

17.3 Concomitant Use of Contact Lenses

Contact lenses should not be worn during the use of this product.

17.4 Concomitant Topical Ocular Therapy

If more than one topical ophthalmic medication is being used, the medicines should be administered at least 5 minutes apart.

Rx Only

©ISTA Pharmaceuticals®, Inc.

Manufactured for: ISTA Pharmaceuticals, Inc.
Irvine, CA 92618

By: Bausch & Lomb Incorporated
Tampa, FL 33637

Under license from:
Senju Pharmaceuticals Co., Ltd.
Osaka, Japan 541-0046

® and ™ marks owned by ISTA Pharmaceuticals, Inc.
Relabeling of additional barcode by:
Physicians Total Care, Inc.
Tulsa, OK 74146

PACKAGE/LABEL PRINCIPAL DISPLAY PANEL

Bromday™

(bromfenac ophthalmic solution) 0.09%

Sterile Rx only

Each mL of Bromday ophthalmic solution contains:

Active: bromfenac sodium hydrate 0.1035%

Preservative: benzalkonium chloride 0.005%

Inactives: boric acid, disodium edetate, polysorbate 80, povidone, sodium borate, sodium sulfite anhydrous, sodium hydroxide to adjust the pH, and water for injection, USP.

This product is sterile when manufactured and should be dispensed in the original unopened container. Instruct patient on precautions to avoid contamination.

For topical application in the eye.

Usual dosage:

Instill one drop into the affected eye(s) once daily beginning 1 day prior to surgery, continued on the day of surgery and through the first 14 days post-surgery.

See accompanying prescribing information.

Store at 15-25°C (59-77°F).